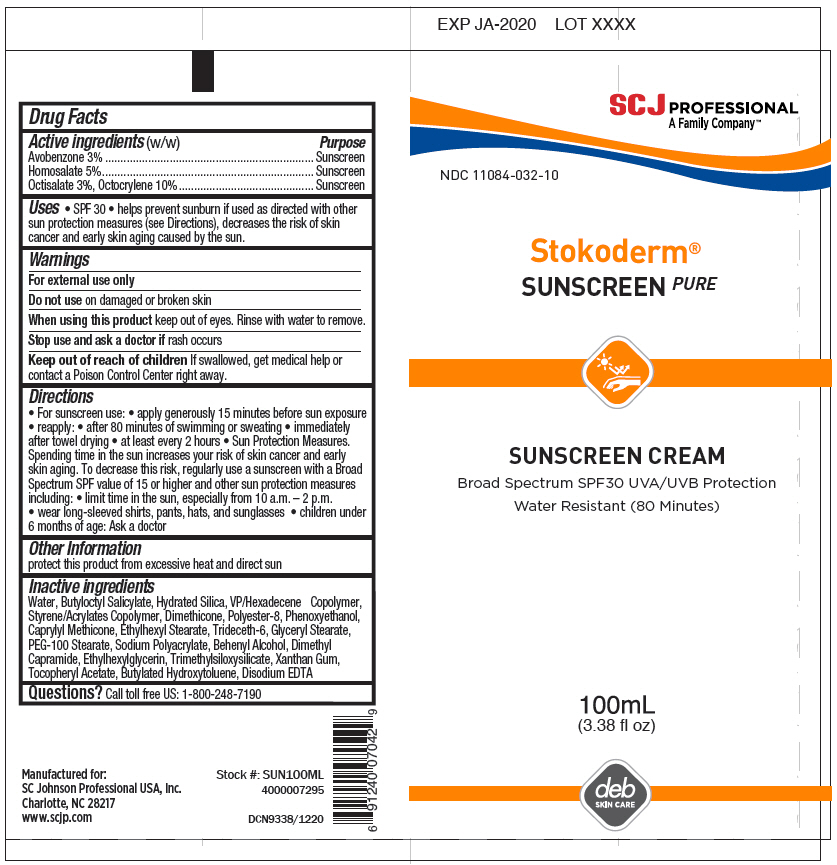 DRUG LABEL: Stokoderm Sunscreen PURE
NDC: 11084-032 | Form: CREAM
Manufacturer: SC Johnson Professional USA, Inc.
Category: otc | Type: HUMAN OTC DRUG LABEL
Date: 20241220

ACTIVE INGREDIENTS: Avobenzone 3 g/100 mL; Octocrylene 10 g/100 mL; Octisalate 3 g/100 mL; Homosalate 5 g/100 mL
INACTIVE INGREDIENTS: WATER; BUTYLOCTYL SALICYLATE; XANTHAN GUM; SODIUM POLYACRYLATE (2500000 MW); STYRENE/ACRYLAMIDE COPOLYMER (500000 MW); EDETATE DISODIUM ANHYDROUS; VINYLPYRROLIDONE/HEXADECENE COPOLYMER; DIMETHICONE; CAPRYLYL TRISILOXANE; ETHYLHEXYL STEARATE; BUTYLATED HYDROXYTOLUENE; GLYCERYL STEARATE SE; TRIDECETH-6; DOCOSANOL; TRIMETHYLSILOXYSILICATE (M/Q 0.8-1.0); POLYESTER-8 (1400 MW, CYANODIPHENYLPROPENOYL CAPPED); DIMETHYL CAPRAMIDE; HYDRATED SILICA; .ALPHA.-TOCOPHEROL ACETATE; PHENOXYETHANOL; ETHYLHEXYLGLYCERIN; PEG-100 STEARATE

Stokoderm® Sunscreen PURE

Drug Facts

ACTIVE INGREDIENT

Active ingredients (w/w) | Purpose
Avobenzone 3% | Sunscreen
Homosalate 5% | Sunscreen
Octisalate 3%, Octocrylene 10% | Sunscreen

Uses

- SPF 30
- helps prevent sunburn if used as directed with other sun protection measures (see Directions), decreases the risk of skin cancer and early skin aging caused by the sun.

Warnings

For external use only

Do not use on damaged or broken skin

When using this product keep out of eyes. Rinse with water to remove.

Stop use and ask a doctor if rash occurs

Keep out of reach of children If swallowed, get medical help or contact a Poison Control Center right away.

Directions

- For sunscreen use:
  - apply generously 15 minutes before sun exposure
- reapply:
  - after 80 minutes of swimming or sweating
  - immediately after towel drying
  - at least every 2 hours
- Sun Protection Measures. Spending time in the sun increases your risk of skin cancer and early skin aging. To decrease this risk, regularly use a sunscreen with a Broad Spectrum SPF value of 15 or higher and other sun protection measures including:
  - limit time in the sun, especially from 10 a.m. – 2 p.m.
  - wear long-sleeved shirts, pants, hats, and sunglasses
  - children under 6 months of age: Ask a doctor

Other Information

protect this product from excessive heat and direct sun

Inactive ingredients

Water, Butyloctyl Salicylate, Hydrated Silica, VP/Hexadecene Copolymer, Styrene/Acrylates Copolymer, Dimethicone, Polyester-8, Phenoxyethanol, Caprylyl Methicone, Ethylhexyl Stearate, Trideceth-6, Glyceryl Stearate, PEG-100 Stearate, Sodium Polyacrylate, Behenyl Alcohol, Dimethyl Capramide, Ethylhexylglycerin, Trimethylsiloxysilicate, Xanthan Gum, Tocopheryl Acetate, Butylated Hydroxytoluene, Disodium EDTA

Questions?

Call toll free US: 1-800-248-7190

PRINCIPAL DISPLAY PANEL - 100 mL Tube Label

EXP JA-2020
LOT XXXX

SCJ PROFESSIONAL
A Family Company™

NDC 11084-032-10

Stokoderm®
SUNSCREEN PURE

SUNSCREEN CREAM
Broad Spectrum SPF30 UVA/UVB Protection
Water Resistant (80 Minutes)

100mL
(3.38 fl oz)

deb
SKIN CARE